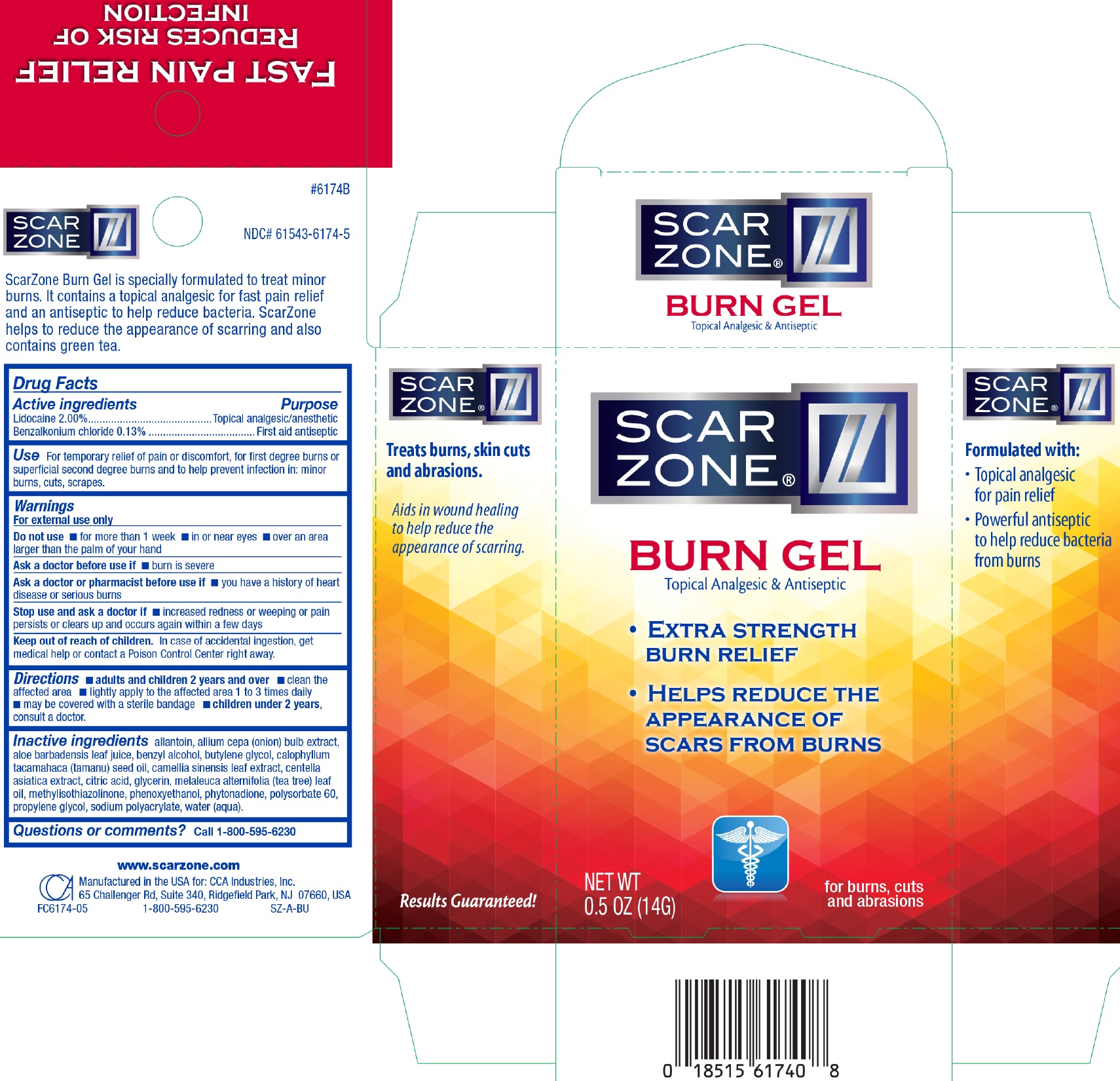 DRUG LABEL: Scar Zone Burn Topical Analgesic and Antiseptic
NDC: 61543-6174 | Form: GEL
Manufacturer: CCA Industries, Inc.
Category: otc | Type: HUMAN OTC DRUG LABEL
Date: 20221216

ACTIVE INGREDIENTS: LIDOCAINE 2 g/100 g; BENZALKONIUM CHLORIDE 0.13 g/100 g
INACTIVE INGREDIENTS: ALLANTOIN; ONION; ALOE VERA LEAF; BENZYL ALCOHOL; BUTYLENE GLYCOL; GREEN TEA LEAF; CENTELLA ASIATICA; CITRIC ACID MONOHYDRATE; GLYCERIN; TEA TREE OIL; METHYLISOTHIAZOLINONE; PHENOXYETHANOL; PHYTONADIONE; POLYSORBATE 60; PROPYLENE GLYCOL; WATER

Scar Zone Burn Gel Topical Analgesic & Antiseptic

Active Ingredients

Lidocaine 2.00%
Benzalkonium Chloride 0.13%

Purpose

Topical Analgesic/Anesthetic
First Aid Antiseptic

Use

For temporary relief of pain or discomfort, for first degree burns or superficial second degree burns and to help prevent infection in: minor burns, cuts, scrapes.

Warnings

- For external use only

Do not use

- for more than 1 week
- in or near eyes
- over an area larger than the palm of your hand

Ask a doctor before use if

burn in severe

Ask a doctor or pharmacist before use if

- you have a history of heart disease or serious burns

Stop use and ask a doctor if

increased redness or weeping or pain persist or clears up and occurs again within a few days

Keep out of reach of children

In case of accidental ingestion, get medical help or contact a Poison Control Center right away.

Directions

adults and children 2 years and over

- clean the affected area
- lightly apply to the affected area 1 to 3 times daily
- may be covered with a sterile bandage
- Children under 2 years, consult a doctor.

Inactive Ingredients

allantoin, allium cepa (onion) bulb extract, aloe barbadensis leaf juice, benzyl alcohol, butylene glycol, calophyllum tacamahaca (tamanu) seed oil, camellia sinensis leaf extract, centella asiatica extract, citric acid, glycerin, melaleuca alternifolia (tea tree) leaf oil, methylisothiazolinone, phenoxyethanol, phytonadione, polysorbate 60, propylene glycol, sodium polyacrylate, water (aqua).

Questions or Comments?

- Call 1-800-595-6230